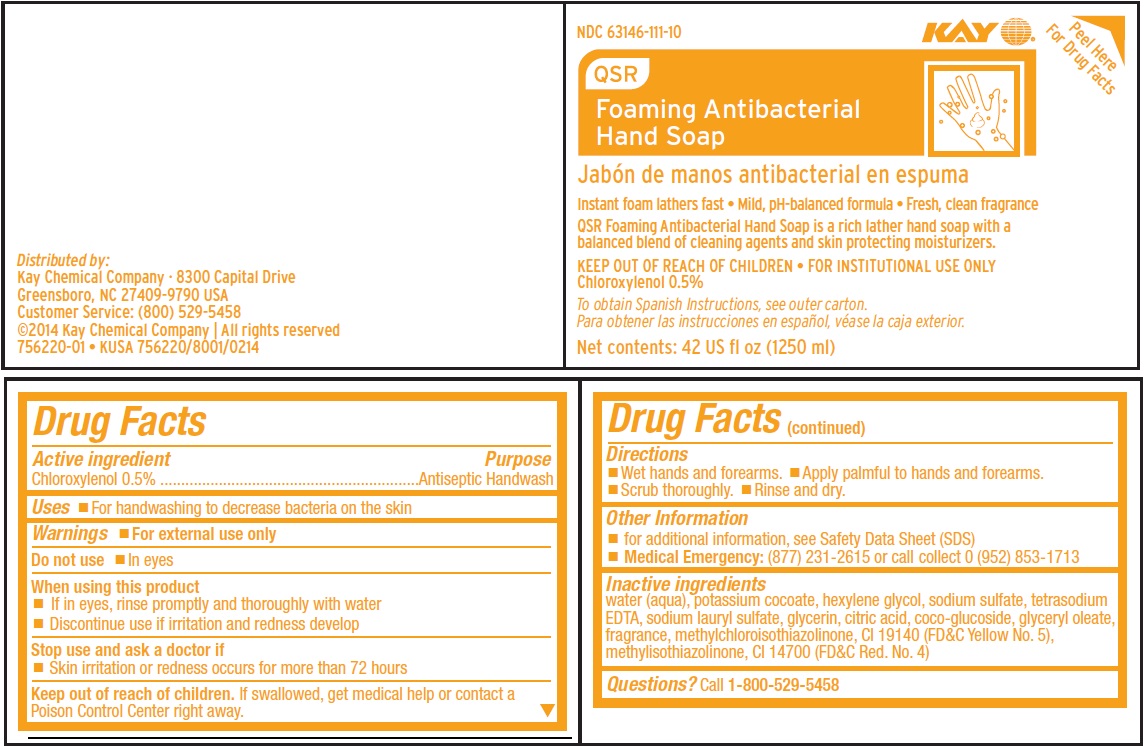 DRUG LABEL: QSR FOAMING ANTIBACTERIAL HANDSOAP
NDC: 47593-672 | Form: SOLUTION
Manufacturer: Ecolab Inc.
Category: otc | Type: HUMAN OTC DRUG LABEL
Date: 20251230

ACTIVE INGREDIENTS: CHLOROXYLENOL 5 mg/1 mL
INACTIVE INGREDIENTS: WATER; POTASSIUM COCOATE; HEXYLENE GLYCOL; SODIUM SULFATE ANHYDROUS; EDETATE SODIUM; SODIUM LAURYL SULFATE; GLYCERIN; ANHYDROUS CITRIC ACID; COCO-GLUCOSIDE; GLYCERYL OLEATE; METHYLCHLOROISOTHIAZOLINONE; FD&C YELLOW NO. 5; METHYLISOTHIAZOLINONE; FD&C RED NO. 4

Drug Facts

Active ingredient

Chloroxylenol, 0.5%

Purpose

Antiseptic handwash

Uses

- For handwashing to decrease bacteria on the skin.

Warnings

- For external use only

Do not use

- In eyes

When using this product

- If in eyes, rinse promptly and thoroughly with water
- Discontinue use if irritation and redness develop

Stop use and ask doctor if

Skin irritation or redness occurs for more than 72 hours

Keep out of reach of children. If swallowed, get medical help or contact a Poison Control Center right away.

Directions

- Wet hands and forearms. • Apply palmful to hands and forearms. • Scrub Thoroughly. • Rinse and dry.

Other Information

- for additional information, see Safety Data Sheet (SDS)
- Medical emergency: (877) 231-2615 or call collect 0 (952) 853-1713

INACTIVE INGREDIENT

Inactive ingredients water (aqua), potassium cocoate, hexylene glycol, sodium sulfate, tetrasodium EDTA, sodium lauryl sulfate, glycerin, citric acid, coco-glucoside, glyceryl oleate, fragrance, methylchloroisothiazolinone, CI 19140 (FD&C Yellow No. 5), methylisothiazolinone, CI 14700 (FD&C Red. No. 4)

Questions?

Questions? Call 1-800-529-5458

Principal Display Panel/Representative Label

NDC 63146-111-10

Kay
QSR

Foaming Antibacterial Hand Soap

Instant foam lathers fast • Mild, pH-balanced formula • Fresh, clean fragrance

QSR Foaming Antibacterial Hand Soap is a rich lather hand soap with a balanced blend of cleaning agents and skin protecting moisturizers.

KEEP OUT OF REACH OF CHILDREN • FOR INSTITUTIONAL USE ONLY
Chloroxylenol 0.5%

Net contents: 42 US fl oz (1250 ml)

Distributed by:
Kay Chemical Company · 8300 Capital Drive
Greensboro, NC 27409-9790 USA
Customer Service: (800) 529-5458
©2014 Kay Chemical Company | All rights reserved
756220-01 • KUSA 756220/8001/0214